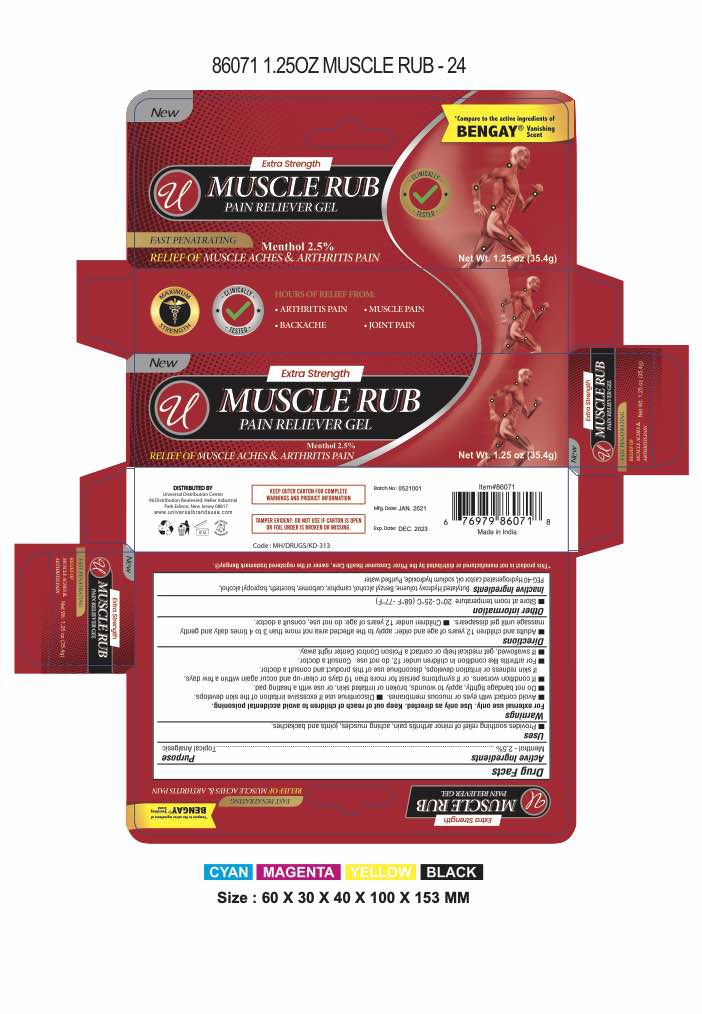 DRUG LABEL: Muscle Rub Pain Reliever Gel
NDC: 52000-072 | Form: GEL
Manufacturer: Universal Distribution Centre LLC
Category: otc | Type: HUMAN OTC DRUG LABEL
Date: 20251030

ACTIVE INGREDIENTS: MENTHOL, UNSPECIFIED FORM 25 mg/1 g
INACTIVE INGREDIENTS: BUTYLATED HYDROXYTOLUENE; CAMPHOR (SYNTHETIC); CARBOMER HOMOPOLYMER, UNSPECIFIED TYPE; ISOCETETH-20; ISOPROPYL ALCOHOL; POLYOXYL 40 HYDROGENATED CASTOR OIL; SODIUM HYDROXIDE; WATER

Pain Reliever Gel

Drug Facts

Active ingredient

Menthol 2.5%

Purpose

Topical analgesic

Uses

temporarily relieves the minor aches and pains of muscles and joints associated with:

- simple backache
- arthritis
- strains
- bruises
- sprains

Warnings

For external use only.

Do not use

- on wounds or damaged skin
- with a heating pad
- on a child under 12 years of age with arthritis-like conditions

Ask a doctor before use if you haveredness over the affected area

When using this product

- avoid contact with eyes or mucous membranes
- do not bandage tightly

Stop use and ask a doctor if

- condition worsens or symptoms persist for more than 7 days
- symptoms clear up and occur again within a few days
- excessive skin irritation occurs

Keep out of reach of children.If swallowed, get medical help or contact a Poison Control Center right away.

Directions

- adults and children 12 years of age and older: apply to affected area not more than 3 to 4 times daily
- children under 12 years of age: ask a doctor

Other information

store at 20° to 25°C (68° to 77°F)

Inactive ingredients

camphor, carbomer, DMDM hydantoin, isoceteth-20, isopropyl alcohol, PEG-40 hydrogenated castor oil, sodium hydroxide, water

Questions?

call 1-800-223-0182(toll-free) or 215-273-8755(collect)

Distributed by:
JOHNSON & JOHNSON
CONSUMER INC.
Skillman, NJ 08558

PRINCIPAL DISPLAY PANEL - 57 g Tube Carton

Extra Strength Muscle Rub

Pain Reliever Gel

Fast Penetrating
MENTHOL 2.5% TOPICAL ANALGESIC GEL

NET WT 1 OZ (35.4 g)